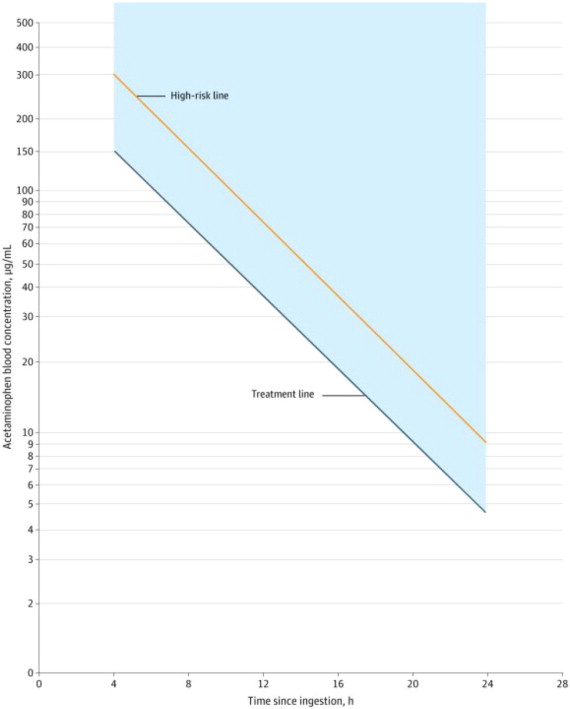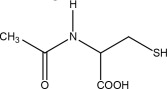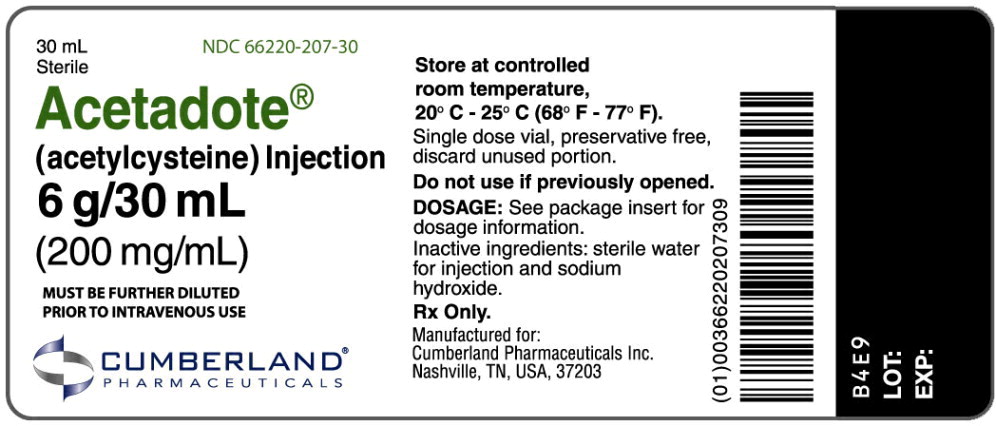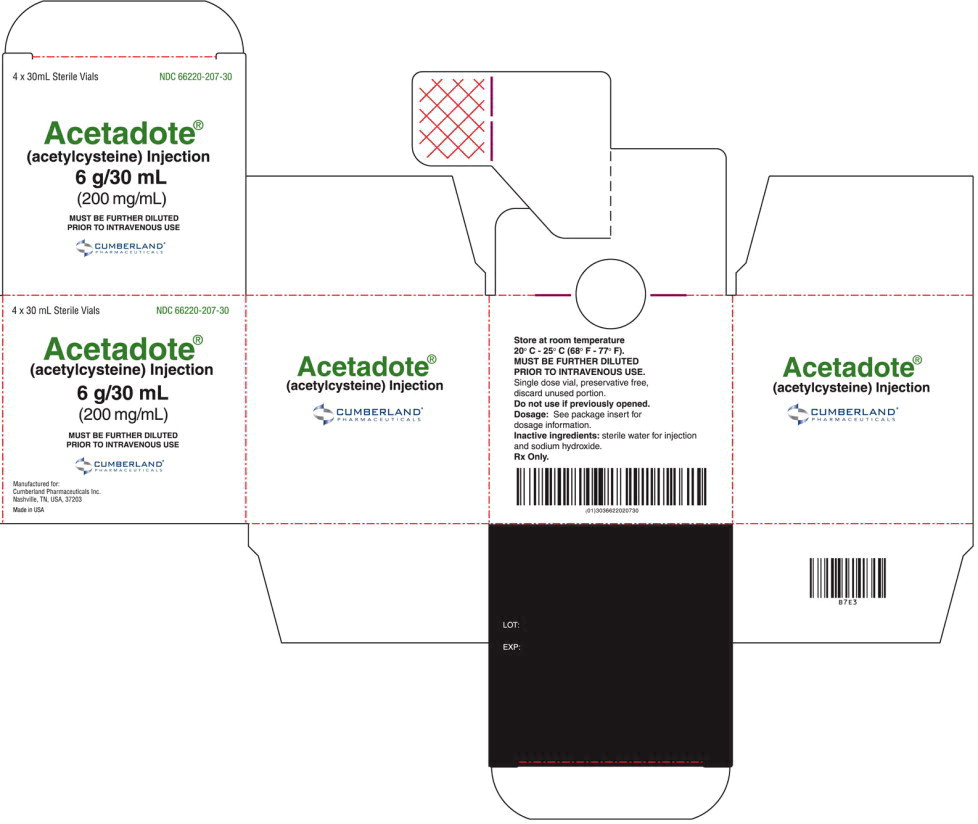 DRUG LABEL: ACETADOTE
NDC: 66220-207 | Form: INJECTION, SOLUTION
Manufacturer: Cumberland Pharmaceuticals Inc.
Category: prescription | Type: HUMAN PRESCRIPTION DRUG LABEL
Date: 20250430

ACTIVE INGREDIENTS: Acetylcysteine 200 mg/1 mL
INACTIVE INGREDIENTS: water; sodium hydroxide; nitrogen

HIGHLIGHTS OF PRESCRIBING INFORMATION

These highlights do not include all the information needed to use ACETADOTE safely and effectively. See full prescribing information for ACETADOTE.
ACETADOTE (acetylcysteine) injection, for intravenous use
Initial U.S. Approval: 2004

RECENT MAJOR CHANGES

Dosage and Administration (2.1, 2.2, 2.3, 2.4, 2.5) | 11/2024

1 INDICATIONS AND USAGE

ACETADOTE is an antidote for acetaminophen overdose indicated to prevent or lessen hepatic injury after ingestion of a potentially hepatotoxic quantity of acetaminophen in adults and pediatric patients who weigh 5 kg or greater with acute ingestion or from repeated supratherapeutic ingestion (RSI) (1).

2 DOSAGE AND ADMINISTRATION

Pre-Treatment Assessment Following Acute Ingestion (2.1):

Prior to initiating treatment with ACETADOTE, decide whether the three-bag or two-bag regimen will be used.

Obtain a plasma or serum sample to assay for acetaminophen concentration at least 4 hours after ingestion.

- If the time of acetaminophen ingestion is unknown:
  - Administer a loading dose of ACETADOTE immediately.
  - Obtain an acetaminophen concentration to determine need for continued treatment.
- If the acetaminophen concentration cannot be obtained (or is unavailable or uninterpretable) within the 8-hour time interval after acetaminophen ingestion or there is clinical evidence of acetaminophen toxicity:
  - Administer a loading dose of ACETADOTE immediately and continue treatment for a total of two doses over 20 hours or three doses over 21 hours (2.5).
- If the patient presents more than 8 hours after ingestion and the time of acute acetaminophen ingestion is known:
  - Administer a loading dose of ACETADOTE immediately
  - Obtain acetaminophen concentration to determine need for continued treatment
- If the patient presents less than 8 hours after ingestion and the time of acute acetaminophen ingestion is known and the acetaminophen concentration is known:
  - Use the revised Rumack-Matthew nomogram (Figure 1) to determine whether or not to initiate treatment with ACETADOTE (2.2)

Nomogram for Estimating Potential for Hepatotoxicity from Acute Acetaminophen Ingestion (2.2):

See Full Prescribing Information for instructions on how to use the nomogram to determine the need for dosing.

Preparation and Storage of Diluted Solution Prior to Administration (2.3):

- Calculate the dose (mg) based on the patient's weight in kg; multiple vials of ACETADOTE may be required.
  - ACETADOTE is hyperosmolar (2,600 mOsmol/L), therefore ACETADOTE must be diluted in the recommended volume of sterile water for injection, 0.45% sodium chloride injection, or 5% dextrose in water injection prior to intravenous administration. In general, 0.45% normal saline is the preferred diluent because it provides a more consistent osmolarity profile, reduces the amount of free water delivered to the patient, and better approximates physiologic fluids.

See Full Prescribing Information for examples of osmolarity depending on the type of solution and ACETADOTE concentration.

General Considerations for Selecting the Three-Bag or Two-Bag Regimen (2.4):

- It is not known whether the two-bag regimen is comparable to the three-bag regimen in preventing hepatotoxicity.
- Patients 40 kg or less should receive the three-bag regimen.
- For patients weighing 41 kg or greater, the three-bag regimen may be preferred for those with early signs of severe liver injury or a large acetaminophen ingestion.

Recommended Dosage for Acute Acetaminophen Ingestion (2.5):

- ACETADOTE is for intravenous administration only
- Total dosage of ACETADOTE is 300 mg/kg given intravenously as either:
  - 3 separate doses infused over a total of 21 hours
    OR
  - 2 separate doses infused over a total of 20 hours.
- See Full Prescribing Information for weight-based dosage and weight-based dilution (2.5)

See Full Prescribing Information for recommendations for continuing ACETADOTE treatment after 21 hours (2.2).

Repeated Supratherapeutic Acetaminophen Ingestion (2.6):

- Obtain acetaminophen concentration and other laboratory tests to guide treatment; revised Rumack-Matthew nomogram does not apply.

3 DOSAGE FORMS AND STRENGTHS

Injection: 6000 mg/30 mL (200 mg/mL) in a single-dose vial (3)

4 CONTRAINDICATIONS

Patients with a previous hypersensitivity reaction to acetylcysteine (4)

5 WARNINGS AND PRECAUTIONS

- Hypersensitivity Reactions: Fatal or life-threatening anaphylaxis, rash, hypotension, wheezing, shortness of breath, and/or bronchospasm have been observed. Observe patients during and after the infusion; immediately discontinue infusion if a serious reaction occurs and initiate appropriate treatment. ACETADOTE infusion may be carefully restarted after treatment of hypersensitivity has been initiated and acute symptoms have resolved (5.1).
- Fluid Overload: Total volume administered should be reduced for patients weighing less than 40 kg and for those requiring fluid restriction (5.2).

6 ADVERSE REACTIONS

Most common adverse reactions (> 2%) are rash, urticaria/facial flushing

and pruritus (6.1).

To report SUSPECTED ADVERSE REACTIONS, contact Cumberland Pharmaceuticals Inc. at 1-877-484-2700 or FDA at 1-800-FDA-1088 or www.fda.gov/medwatch.

FULL PRESCRIBING INFORMATION

1 INDICATIONS AND USAGE

ACETADOTE is indicated to prevent or lessen hepatic injury after ingestion of a potentially hepatotoxic quantity of acetaminophen in adults and pediatric patients who weigh 5 kg or greater with acute ingestion or from repeated supratherapeutic ingestion (RSI).

2 DOSAGE AND ADMINISTRATION

2.1 Pre-Treatment Assessment and Testing Following Acute Acetaminophen Ingestion

Prior to initiating treatment with ACETADOTE, decide whether the three-bag or two-bag regimen will be used [see Dosage and Administration (2.4)].

The following recommendations are related to acute acetaminophen ingestion. For recommendations related to repeated supratherapeutic exposure [see Dosage and Administration (2.6)].

1. Assess the history and timing of acetaminophen ingestion as an overdose.
  - The reported history of the quantity of acetaminophen ingested as an overdose is often inaccurate and is not a reliable guide to therapy.
2. Obtain the following laboratory tests to monitor hepatic and renal function and electrolyte and fluid balance: aspartate aminotransferase (AST), alanine aminotransferase (ALT), bilirubin, international normalized ratio (INR), creatinine, blood urea nitrogen (BUN), blood glucose, and electrolytes.
3. Obtain a plasma or serum sample to assay for acetaminophen concentration at least 4 hours after ingestion. Acetaminophen concentrations obtained earlier than 4 hours post-ingestion may be misleading as they may not represent maximum acetaminophen concentrations.
4. If the time of acute acetaminophen ingestion is unknown:
  - Administer a loading dose of ACETADOTE immediately [see Dosage and Administration (2.5)].
  - Obtain an acetaminophen concentration to determine need for continued treatment [see Dosage and Administration (2.2)].
5. If the acetaminophen concentration cannot be obtained (or is unavailable or uninterpretable) within the 8-hour time interval after acetaminophen ingestion or there is clinical evidence of acetaminophen toxicity:
  - Administer a loading dose of ACETADOTE immediately and continue treatment for a total of two doses over 20 hours or three doses over 21 hours [see Dosage and Administration (2.5)].
6. If the patient presents more than 8 hours after ingestion and the time of acute acetaminophen ingestion is known:
  - Administer a loading dose of ACETADOTE immediately [see Dosage and Administration (2.5)]
  - Obtain an acetaminophen concentration to determine need for continued treatment [see Dosage and Administration (2.2)].
7. If the patient presents less than 8 hours after ingestion and the time of acute acetaminophen ingestion is known and the acetaminophen concentration is known:
  - Use the revised Rumack-Matthew nomogram (Figure 1) to determine whether or not to initiate treatment with ACETADOTE [see Dosage and Administration (2.2)].

2.2 Nomogram for Estimating Potential for Hepatoxicity from Acute Acetaminophen Ingestion and Need for ACETADOTE Treatment

ACETADOTE is an antidote for acetaminophen overdose. The critical ingestion-treatment interval for maximal protection against severe hepatic injury is between 0 and 8 hours. Efficacy diminishes progressively after 8 hours and treatment initiation between 15 and 24 hours post-ingestion of acetaminophen yields limited efficacy. However, it does not appear to worsen the condition of patients and it should not be withheld, since the reported time of ingestion may not be correct.

If the timing of the acute acetaminophen ingestion is known and the results of the acetaminophen assay are available within 8 hours:

- Refer to the revised Rumack-Matthew nomogram (see Figure 1) to determine whether or not to initiate treatment with ACETADOTE.
- Initiation of ACETADOTE depends on the plasma or serum acetaminophen concentration and also the clinical presentation of the patient.

The nomogram may underestimate the hepatotoxicity risk in patients with chronic alcoholism, malnutrition, or CYP2E1 enzyme inducing drugs (e.g., isoniazid), and consideration should be given to treating these patients even if the acetaminophen concentrations are in the nontoxic range.

Loading dose

For patients whose acetaminophen concentrations are at or above the treatment line (see Figure 1):

- Administer a loading dose of ACETADOTE [see Dosage and Administration (2.5)].

For patients with an acute overdose from an extended-release acetaminophen, if the acetaminophen concentration at 4 hours post ingestion is below the treatment line (see Figure 1) then obtain a second sample for acetaminophen concentration 8 to 10 hours after the acute ingestion. If the second value is at or above the treatment line:

- Administer a loading dose of ACETADOTE [see Dosage and Administration (2.5)].

For patients whose values are below the treatment line (see Figure 1), but time of ingestion was unknown or sample was obtained less than 4 hours after ingestion:

- Administer a loading dose of ACETADOTE [see Dosage and Administration (2.5)].

For patients whose values are below the treatment line (see Figure 1) and time of ingestion is known and the sample was obtained more than 4 hours after ingestion, do not administer ACETADOTE because there is minimal risk of hepatotoxicity.

Figure 1. Revised Rumack-Matthew Nomogram for Estimating Risk of Hepatoxicity After Acute Ingestion of Acetaminophen

Maintenance Dose

Determine the need for continued treatment with ACETADOTE after the loading dose. Choose ONE of the following based on the acetaminophen concentration:

The acetaminophen concentration is above the treatment line (see Figure 1) according to the nomogram:

- Continue ACETADOTE treatment with the maintenance dose for a total of either two or three separate doses over an infusion time of 20 or 21 hours, respectively [see Dosage and Administration (2.5)].
- Monitor hepatic and renal function and electrolytes throughout treatment.

The acetaminophen concentration could not be obtained:

- Continue ACETADOTE treatment with the maintenance dose for a total of either two or three separate doses over an infusion time of 20 or 21 hours, respectively [see Dosage and Administration (2.5)].
- Monitor hepatic and renal function and electrolytes throughout treatment.

For patients whose acetaminophen concentration is below the treatment line (see Figure 1) and time of ingestion is known and the sample was obtained more than 4 hours after ingestion:

- Discontinue ACETADOTE.

The acetaminophen concentration was in the non-toxic range, but time of ingestion was unknown or less than 4 hours:

- Obtain a second sample for acetaminophen concentration and consider the patient's clinical status to decide whether or not to continue ACETADOTE treatment.
- If there is any uncertainty as to patient's risk of developing hepatotoxicity, it is recommended to administer a complete treatment course.

Continued Therapy After Completion of Loading and Maintenance Doses

In cases of suspected massive overdose, or with concomitant ingestion of other substances, or in patients with preexisting liver disease; the absorption and/or the half-life of acetaminophen may be prolonged. In such cases, consideration should be given to the need for continued treatment with ACETADOTE beyond the total 300 mg/kg dose.

Acetaminophen levels and ALT/AST and INR should be checked after the last maintenance dose. If acetaminophen levels are still detectable, or if the ALT/AST are still increasing or the INR remains elevated; dosing should be continued and the treating physician should contact a US regional poison center at 1-800-222-1222, alternatively, a “special health professional assistance line for acetaminophen overdose” at 1-800-525-6115 for assistance with dosing recommendations, or 1-877-484-2700 for additional information.

2.3 Preparation and Storage of ACETADOTE Diluted Solution Prior to Administration

Refer to Table 2 and Table 3 to calculate the dose (mg) based on the patient's weight in kg; multiple vials of ACETADOTE may be required [see Dosage and Administration (2.5)]. Discard any unused portion left in the vial.

Because ACETADOTE is hyperosmolar (2,600 mOsmol/L), ACETADOTE must be diluted in the recommended volume of sterile water for injection, 0.45% sodium chloride injection (1/2 normal saline), or 5% dextrose in water prior to intravenous administration. The total injection volume will vary based on the patient's weight and chosen dosage regimen (i.e., three-bag or two-bag) [see Dosage and Administration (2.5), Warnings and Precautions (5.2)].

The choice of diluent should be based on the individual patient's clinical status, concurrent medical conditions, and institutional protocols. The treating clinician should assess each case individually and consult with their pharmacy if there are any concerns about the appropriate diluent choice. In general, 0.45% normal saline is the preferred diluent because it provides a more consistent osmolarity profile, reduces the amount of free water delivered to the patient, and better approximates physiologic fluids than 5% dextrose in water or sterile water for injection. However, consider 5% dextrose in water or sterile water for injection if sodium load is a concern for the patient.

Dilution of ACETADOTE in each of these three solutions results in different osmolarity of the acetylcysteine solution for intravenous administration (see Table 1 for examples of different osmolarity of the solution depending on the type of solution and the ACETADOTE concentration).

Table 1. Examples of Acetylcysteine Concentration and Osmolarity in Three Solutions
Acetylcysteine Concentration | Osmolarity
Acetylcysteine Concentration | Sterile Water for Injection | 0.45% Sodium Chloride Injection | 5% Dextrose in Water (D5W)
4 mg/mL (lowest concentration 3-bag protocol) | 52 mOsmol/L* | 194 mOsmol/L | 311 mOsmol/L
54.5 mg/mL (highest concentration 3-bag protocol) | 744 mOsmol/L | 855 mOsmol/L | 957 mOsmol/L
7.9 mg/mL (lowest concentration 2-bag protocol) | 105 mOsmol/L | 241 mOsmol/L | 360 mOsmol/L
18.2 mg/mL (highest concentration 2-bag protocol) | 239 mOsmol/L | 368 mOsmol/L | 487 mOsmol/L
* Adjust osmolarity to a physiologically safe level (generally not less than 150 mOsmol/L in pediatric patients).

The choice of diluent should be based on the individual patient's clinical status, concurrent medical conditions, and institutional protocols. The treating clinician should assess each case individually and consult with their pharmacy if there are any concerns about the appropriate diluent choice. In general, 0.45% normal saline is the preferred diluent, as it provides a more consistent osmolarity profile, reduces the amount of free water delivered to the patient, and better approximates physiologic fluids than 5% dextrose in water or sterile water for injection.

Visually inspect for particular matter and discoloration prior to administration. The color of the diluted solution ranges from colorless to a slight pink or purple once the stopper is punctured (the color change does not affect the quality of the product). The diluted solution can be stored for 24 hours at room temperature. Discard the unused portion. If a vial was previously opened, do not use for intravenous administration.

2.4 General Considerations for Selecting the Three-Bag or Two-Bag Regimen

The total recommended dosage of ACETADOTE is 300 mg/kg given intravenously as either a three-bag regimen or a two-bag regimen [see Dosage and Administration (2.5)].

It is not known whether the two-bag regimen is comparable to the three-bag regimen for efficacy in preventing hepatotoxicity.

There are insufficient data to recommend use of the two-bag regimen in patients 40 kg or less; these patients should receive the three-bag regimen.

For patients weighing 41 kg or greater, the clinician should consider the following factors when deciding whether to select the three-bag or two-bag regimen:

- The three-bag regimen administers more ACETADOTE in the first three hours and may be preferred for patients with early signs of severe liver injury or history of a large acetaminophen ingestion; however, there is the potential for a higher incidence of hypersensitivity reactions.
- The two-bag regimen delivers a lower amount of ACETADOTE over the first three hours and may be associated with fewer hypersensitivity reactions than the three-bag regimen [see Adverse Reactions (6.2), Clinical Studies (14)].

2.5 Recommended Dosage for Acute Acetaminophen Ingestion

ACETADOTE is for intravenous administration only.

The total recommended dosage of ACETADOTE is 300 mg/kg given intravenously as either a three-bag regimen administered as a loading, second, and third dose infused over a total of 21 hours or a two-bag regimen administered as a loading and second dose infused over a total of 20 hours.

For the recommended weight-based dosage and weight-based dilution in patients see Table 2 for the three-bag regimen (for patients 5 kg or greater) or Table 3 for the two-bag regimen (for patients 41 kg or greater).

Three-Bag Regimen

Table 2. Three-Bag Recommended ACETADOTE Dosage and Dilution for Patients 5 kg or greater
Body Weight | Bag 1 (Loading Dose) |  |  | Bag 2 (Second Dose) |  |  | Bag 3 (Third Dose)
Body Weight | Loading Dose | Diluent Volume* | Infusion time | Second Dose | Diluent Volume* | Infusion time | Third Dose | Diluent Volume* | Infusion time
5 kg** to 20 kg | 150 mg/kg | 3 mL/kg | Infused over 1 hour | 50 mg/kg | 7 mL/kg | Infused over 4 hours | 100 mg/kg | 14 mL/kg | Infused over 16 hours
21 kg to 40 kg | 150 mg/kg | 100 mL | Infused over 1 hour | 50 mg/kg | 250 mL | Infused over 4 hours | 100 mg/kg | 500 mL | Infused over 16 hours
41 kg to 99 kg | 150 mg/kg | 200 mL | Infused over 1 hour | 50 mg/kg | 500 mL | Infused over 4 hours | 100 mg/kg | 1,000 mL | Infused over 16 hours
100 kg or greater*** | 15,000 mg | 200 mL | Infused over 1 hour | 5,000 mg | 500 mL | Infused over 4 hours | 10,000 mg | 1,000 mL | Infused over 16 hours
* Dilute ACETADOTE in one of the following three solutions: sterile water for injection, 0.45% sodium chloride injection, or 5% dextrose in water.
**Recommended dosing for those less than 5 kg has not been studied.
***No specific studies have been conducted to evaluate the necessity of dose adjustments in patients weighing over 100 kg. Limited information is available regarding the dosing requirements of patients that weigh more than 100 kg.

Two-Bag Regimen

Table 3. Alternative Regimen for Patients 41 kg or Greater: Two-Bag Recommended ACETADOTE Dosage and Dilution
Body Weight | Bag 1 (Loading Dose) |  |  | Bag 2 (Second Dose)
Body Weight | Loading Dose | Diluent Volume* | Infusion time | Second Dose | Diluent Volume* | Infusion time
41 kg to 99 kg | 200 mg/kg | 1,000 mL | Infused over 4 hours | 100 mg/kg | 500 mL | Infused over 16 hours
100 kg or greater** | 20,000 mg | 1,000 mL | Infused over 4 hours | 10,000 mg | 500 mL | Infused over 16 hours
*Dilute ACETADOTE in one of the following three solutions: sterile water for injection, 0.45% sodium chloride injection, or 5% dextrose in water.
**No specific studies have been conducted to evaluate the necessity of dose adjustments in patients weighing over 100 kg. Limited information is available regarding the dosing requirements of patients that weigh more than 100 kg.

2.6 Recommendations for Repeated Supratherapeutic Acetaminophen Ingestion

Repeated supratherapeutic acetaminophen ingestion (RSI) is an ingestion of acetaminophen at dosages higher than those recommended for extended periods of time. The risk of hepatotoxicity and the recommendations for treatment of acute acetaminophen ingestion (i.e., the revised Rumack-Matthew nomogram) do not apply to patients with RSI. Therefore, obtain the following information to guide ACETADOTE treatment for RSI:

Repeated supratherapeutic acetaminophen ingestion (RSI) is an ingestion of acetaminophen at dosages higher than those recommended for extended periods of time. The risk of hepatotoxicity and the recommendations for treatment of acute acetaminophen ingestion (i.e., the revised Rumack-Matthew nomogram) do not apply to patients with RSI. Therefore, obtain the following information to guide ACETADOTE treatment for RSI:

- Acetaminophen serum or plasma concentrations. A reported history of the quantity of acetaminophen ingested is often inaccurate and is not a reliable guide to therapy.
- Laboratory tests to monitor hepatic and renal function and electrolyte and fluid balance: AST, ALT, bilirubin, INR, creatinine, BUN, blood glucose, and electrolytes.

For specific ACETADOTE dosage and administration information in patients with RSI, consider contacting your regional poison center at 1-800-222-1222, or alternatively, a special health professional assistance line for acetaminophen overdose at 1-800-525-6115.

3 DOSAGE FORMS AND STRENGTHS

Injection: 6000 mg/30 mL (200 mg/mL) of acetylcysteine in a single-dose vial.

4 CONTRAINDICATIONS

ACETADOTE is contraindicated in patients with a previous hypersensitivity reaction to acetylcysteine [see Warnings and Precautions (5.1)].

5 WARNINGS AND PRECAUTIONS

5.1 Hypersensitivity Reactions

Serious acute hypersensitivity reactions; including fatal or life-threatening anaphylaxis, rash, hypotension, wheezing, and/or shortness of breath; have been observed in patients receiving intravenous acetylcysteine for acetaminophen overdose and occurred soon after initiation of the infusion [see Adverse Reactions (6)]. If a severe hypersensitivity reaction occurs, immediately stop the infusion of ACETADOTE and initiate appropriate treatment.

Patients with asthma should be closely monitored during initiation of ACETADOTE therapy and throughout ACETADOTE therapy.

Acute flushing and erythema of the skin may occur in patients receiving acetylcysteine intravenously. These reactions usually occur 30 to 60 minutes after initiating the infusion and often resolve spontaneously despite continued infusion of acetylcysteine. If a reaction to acetylcysteine involves more than simply flushing and erythema of the skin, it should be treated as a hypersensitivity reaction.

Management of less severe hypersensitivity reactions should be based upon the severity of the reaction and include temporary interruption of the infusion and/or administration of antihistaminic drugs. The ACETADOTE infusion may be carefully restarted after treatment of the hypersensitivity symptoms has been initiated and acute symptoms have resolved; however, if the hypersensitivity reaction returns upon re-initiation of treatment or increases in severity, ACETADOTE should be discontinued and alternative patient management should be considered.

5.2 Fluid Overload

The total volume of ACETADOTE administered should be adjusted for patients less than 40 kg and for those requiring fluid restriction.

Intravenous administration of ACETADOTE can cause fluid overload, potentially resulting in hyponatremia, seizure, and death. To avoid fluid overload, use the recommended dilutions [see Dosage and Administration (2.5)].

6 ADVERSE REACTIONS

6.1 Clinical Studies Experience

The following clinically significant adverse reactions are described elsewhere in labeling:

- Hypersensitivity Reactions [see Warnings and Precautions (5.1)]
- Fluid Overload [see Warnings and Precautions (5.2)]

Because clinical trials are conducted under widely varying conditions, adverse reaction rates observed in the clinical trials of a drug cannot be directly compared to rates in the clinical trials of another drug and may not reflect the rates observed in practice.

In the literature, the most frequently reported adverse reactions attributed to intravenous acetylcysteine administration were rash, urticaria and pruritus. The frequency of adverse reactions has been reported to be between 0.2% and 21%, and they most commonly occur during the initial loading dose of acetylcysteine.

Loading Dose/Infusion Rate Study

In a randomized, open-label, multi-center clinical study conducted in Australia in patients with acetaminophen poisoning, the rates of hypersensitivity reactions between a 15-minute and 60-minute intravenous infusion for the 150 mg/kg loading dose of acetylcysteine were compared.

The incidence of drug-related adverse reactions occurring within the first 2 hours following acetylcysteine administration is presented in Table 4. Overall, 17% of patients developed an acute hypersensitivity reaction (18% in the 15-minute infusion group; 14% in the 60-minute infusion group) [see Warnings and Precautions (5.1), Clinical Studies (14)].

Table 4. Incidence of Drug-Related Adverse Reactions Occurring Within the First 2 Hours Following Study Drug Administration by Preferred Term: Loading Dose/Infusion Rate Study
Treatment Group | 15-minutes |  |  |  | 60-minutes
Number of Patients | n=109 |  |  |  | n=71
Cardiac disorders | 5 (5%) |  |  |  | 2 (3%)
Severity: | Unkn | Mild | Moderate | Severe | Unkn | Mild | Moderate | Severe
Tachycardia NOS |  | 4 (4%) | 1 (1%) |  |  | 2 (3%)
Gastrointestinal disorders | 16 (15%) |  |  |  | 7 (10%)
Severity: | Unkn | Mild | Moderate | Severe | Unkn | Mild | Moderate | Severe
Nausea | 1 (1%) |  | 6 (6%) |  |  | 1 (1%) | 1 (1%)
Vomiting NOS |  | 2 (2%) | 11 (10%) |  |  | 2 (3%) | 4 (6%)
Immune System Disorders | 20 (18%) |  |  |  | 10 (14%)
Severity: | Unkn | Mild | Moderate | Severe | Unkn | Mild | Moderate | Severe
Hypersensitivity reaction | 2 (2%) | 6 (6%) | 11 (10%) | 1 (1%) |  | 4 (6%) | 5 (7%) | 1 (1%)
Respiratory, thoracic and mediastinal disorders | 2 (2%) |  |  |  | 2 (3%)
Severity: | Unkn | Mild | Moderate | Severe | Unkn | Mild | Moderate | Severe
Pharyngitis |  |  | 1 (1%)
Rhinorrhea |  | 1 (1%)
Rhonchi |  |  |  |  |  | 1 (1%)
Throat tightness |  |  |  |  |  | 1 (1%)
Skin & subcutaneous tissue disorders | 6 (6%) |  |  |  | 5 (7%)
Severity: | Unkn | Mild | Moderate | Severe | Unkn | Mild | Moderate | Severe
Pruritus |  | 1 (1%) |  |  |  | 2 (3%)
Rash NOS |  | 3 (3%) | 2 (2%) |  |  | 3 (4%)
Vascular disorders | 2 (2%) |  |  |  | 3 (4%)
Severity: | Unkn | Mild | Moderate | Severe | Unkn | Mild | Moderate | Severe
Flushing |  | 1 (1%) | 1 (1%) |  |  | 2 (3%) | 1 (1%)
Unkn= Unknown; NOS= not otherwise specified

Safety Study

A large multi-center study was performed in Canada where data were collected from patients who were treated with intravenous acetylcysteine for acetaminophen overdose between 1980 and 2005. This study evaluated 4709 adult cases and 1905 pediatric cases. The incidence of hypersensitivity reactions in adult (overall incidence 8%) and pediatric (overall incidence 10%) patients is presented in Table 5 and Table 6.

Table 5. Distribution of reported hypersensitivity reactions in adult patients receiving intravenous acetylcysteine
Reaction | Incidence (%) n=4709
Urticaria/Facial Flushing | 6.1%
Pruritus | 4.3%
Respiratory Symptoms* | 1.9%
Edema | 1.6%
Hypotension | 0.1%
Anaphylaxis | 0.1%
*Respiratory symptoms are defined as presence of any of the following: cough, wheezing, stridor, shortness of breath, chest tightness, respiratory distress, or bronchospasm.

Table 6. Distribution of reported hypersensitivity reactions in pediatric patients receiving intravenous acetylcysteine
Reaction | Incidence (%) n=1905
Urticaria/Facial Flushing | 7.6%
Pruritus | 4.1%
Respiratory Symptoms* | 2.2%
Edema | 1.2%
Anaphylaxis | 0.2%
Hypotension | 0.1%
*Respiratory symptoms are defined as presence of any of the following: cough, wheezing, stridor, shortness of breath, chest tightness, respiratory distress, or bronchospasm.

6.2 Postmarketing Experience

Adverse Reactions from Observational Studies

Observational studies from published literature have described rates of hypersensitivity reactions identified by retrospective chart review in subjects receiving the two-bag regimen after adoption of this regimen as institutional policy in three non-US settings and one US setting compared to a historical control group that received the three-bag regimen.

Table 7 displays the incidence of hypersensitivity reactions in patients who received two-bag or three-bag regimens of intravenous acetylcysteine admitted between 2009 to 2020.

Table 7. Incidence of Hypersensitivity Reactions in Patients who Received Two-bag or Three-bag Regimens of Intravenous Acetylcysteine in Published Literature
Study | Hypersensitivity Reactions in Patients Receiving Two-Bag Regimen | Hypersensitivity Reactions in Patients Receiving Three-Bag Regimen
Study 1 (Three Danish hospitals) | 4% (19/507) | 16% (47/292)
Study 2 (Four Australian hospitals) | 5% (8/163) | 14% (45/313)
Study 3 (Nine Australian hospitals) | 1% (17/1300) | 7% (65/911)
Study 4 (One US hospital) | 19% (18/93) | 23% (34/150)

Adverse Reactions from Postmarketing Spontaneous Reports

The following adverse reactions have been identified during post-approval use of ACETADOTE. Because these reactions are reported voluntarily from a population of uncertain size, it is not always possible to reliably estimate their frequency or establish a causal relationship to drug exposure.

Immune system disorders: fatal anaphylaxis

8 USE IN SPECIFIC POPULATIONS

8.1 Pregnancy

Risk Summary

Limited published case reports and case series of pregnant women exposed to acetylcysteine during various trimesters are not sufficient to inform any drug associated risk. Delaying treatment of acetaminophen overdose may increase the risk of maternal or fetal morbidity and mortality [see Clinical Considerations]. Reproduction studies in rats and rabbits following oral administration of acetylcysteine during the period of organogenesis at doses similar to the total intravenous dose (based on the body surface area) did not cause any adverse effects to the fetus. The estimated background risk of major birth defects and miscarriage for the indicated population is unknown. In the U.S. general population, the estimated background risk of major birth defects and miscarriage in clinically recognized pregnancies is 2% to 4% and 15% to 20%, respectively.

Clinical Considerations

Disease-Associated Maternal and/or Embryo/Fetal Risk

Acetaminophen and acetylcysteine cross the placenta. Delaying treatment in pregnant women with acetaminophen overdose and potentially toxic acetaminophen plasma levels may increase the risk of maternal and fetal morbidity and mortality.

Data

Animal Data

Reproduction studies have been performed following administration of acetylcysteine during the period of organogenesis in rats at oral doses up to 2000 mg/kg/day (1.1 times the recommended total human intravenous dose of 300 mg/kg based on body surface area comparison) and in rabbits at oral doses up to 1000 mg/kg/day (1.1 times the recommended total human intravenous dose of 300 mg/kg based on body surface area comparison). No adverse developmental outcomes due to acetylcysteine were observed.

8.2 Lactation

Risk Summary

There are no data on the presence of acetylcysteine in human milk, the effects on the breastfed infant, or the effects on milk production. The developmental and health benefits of breastfeeding should be considered along with the mother's clinical need for ACETADOTE and any potential adverse effects on the breastfed child from ACETADOTE or from the underlying maternal condition.

Clinical Considerations

Based on the pharmacokinetic data, acetylcysteine should be nearly completely cleared 30 hours after administration. Breastfeeding women may consider pumping and discarding their milk for 30 hours after administration.

8.4 Pediatric Use

Safety and effectiveness of ACETADOTE in pediatric patients have not been established by adequate and well-controlled studies. Use of ACETADOTE in pediatric patients 5 kg and greater is based on clinical practice [see Dosage and Administration (2.5)].

10 OVERDOSAGE

Fatal and life-threatening adverse events have been reported following acetylcysteine overdosage, including anaphylaxis, cerebral edema, and hemolytic-uremic syndrome (HUS). Stop acetylcysteine administration in the setting of suspected acetylcysteine overdosage and manage as clinically indicated.

Anaphylaxis, including cases with a fatal outcome, has been reported following acetylcysteine overdosage. Patients who experienced anaphylaxis following acetylcysteine overdosage often became symptomatic during the loading dose and experienced hypotension, rash, angioedema, bronchospasm, or respiratory distress. Cases of anaphylaxis with acetylcysteine overdosage also described coagulopathy, renal failure, or respiratory failure.

Cerebral edema, including cases with a fatal outcome, has been reported following acetylcysteine overdosage. Patients who experienced cerebral edema following acetylcysteine overdose presented with altered mental status, abnormal pupillary responses, seizures. Some cases of cerebral edema with acetylcysteine overdosage described brain herniation.

HUS has been reported following acetylcysteine overdosage. Patients who experienced HUS presented with microangiopathic hemolytic anemia, thrombocytopenia, and acute kidney injury.

Removal of acetylcysteine via hemodialysis has been reported in the literature outside of the context of acetylcysteine overdosage. Studies of hemodialysis in acetaminophen overdose report significant extracorporeal removal of acetylcysteine during hemodialysis. Contact the Poison Center (1-800-222-1222) for overdosage management recommendations for ACETADOTE including considerations for hemodialysis.

11 DESCRIPTION

Acetylcysteine injection is an intravenous antidote for the treatment of acetaminophen overdose. Acetylcysteine is the nonproprietary name for the N-acetyl derivative of the naturally occurring amino acid, L-cysteine (N-acetyl-L-cysteine,). The compound is a white crystalline powder, which melts in the range of 104° to 110°C and has a very slight odor.

The molecular formula of the compound is C5H9NO3S, and its molecular weight is 163.2. Acetylcysteine has the following structural formula:

ACETADOTE is supplied as a sterile solution in vials containing 20% w/v (200 mg/mL) acetylcysteine. The pH of the solution ranges from 6.0 to 7.5. ACETADOTE contains the following inactive ingredients: sodium hydroxide (used for pH adjustment), and Water for Injection, USP.

The amount of sodium in ACETADOTE is approximately 30 mg/mL. Because ACETADOTE is administered based on a patient's weight, the amount of sodium administered in a course of treatment will vary from approximately 225 mg to 4500 mg. The use of ½ normal saline will contribute approximately an additional 1770 mg of sodium per liter of diluent.

12 CLINICAL PHARMACOLOGY

12.1 Mechanism of Action

Acetylcysteine has been shown to reduce the extent of liver injury following acetaminophen overdose. Acetaminophen doses of 150 mg/kg or greater have been associated with hepatotoxicity. Acetylcysteine probably protects the liver by maintaining or restoring the glutathione levels, or by acting as an alternate substrate for conjugation with, and thus detoxification of, the reactive metabolite of acetaminophen.

12.3 Pharmacokinetics

After a single intravenous dose of acetylcysteine, the plasma concentration of total acetylcysteine declined in a poly-exponential decay manner with a mean terminal half-life (T1/2) of 5.6 hours. The mean clearance (CL) for acetylcysteine was 0.11 liter/hr/kg and renal CL constituted about 30% of the total CL.

Distribution:

The steady-state volume of distribution (Vdss) following administration of an intravenous dose of acetylcysteine was 0.47 liter/kg. The protein binding of acetylcysteine ranges from 66 to 87%.

Elimination:

Metabolism:

Acetylcysteine (i.e., N-acetylcysteine) is postulated to form cysteine and disulfides (N,N-diacetylcysteine and N-acetylcysteine). Cysteine is further metabolized to form glutathione and other metabolites.

Excretion:

After a single oral dose of [^35S]-acetylcysteine 100 mg, between 13 to 38% of the total radioactivity administered was recovered in urine within 24 hours. In a separate study, renal clearance was estimated to be approximately 30% of total body clearance.

Specific Populations:

Hepatic Impairment:

Following a 600 mg intravenous dose of acetylcysteine to subjects with mild (Child Pugh Class A, n=1), moderate (Child-Pugh Class B, n=4) or severe (Child-Pugh Class C; n=4) hepatic impairment and 6 healthy matched controls, mean T1/2 increased by 80%. Also, the mean CL decreased by 30% and the systemic acetylcysteine exposure (mean AUC) increased 1.6-fold in subjects with hepatic impairment compared to subjects with normal hepatic function. These changes are not considered to be clinically meaningful.

Renal Impairment:

Hemodialysis may remove some of total acetylcysteine.

13 NONCLINICAL TOXICOLOGY

13.1 Carcinogenesis, Mutagenesis, Impairment of Fertility

Carcinogenesis

Long-term studies in animals have not been performed to evaluate the carcinogenic potential of acetylcysteine.

Mutagenesis

Acetylcysteine was not genotoxic in the Ames test or the in vivo mouse micronucleus test. It was, however, positive in the in vitro mouse lymphoma cell (L5178Y/TK+/-) forward mutation test.

Impairment of Fertility

In a fertility study of acetylcysteine in rats, intravenous administration of 1,000 mg/kg/day (0.5 times the recommended human dose of 300 mg/kg based on body surface area) caused a profound reduction of fertility in females, which was correlated with morphological changes in oocytes and severe impairment of implantation (18 of 20 mated females had no implantations). The reversibility of this effect was not evaluated. No effects on fertility were observed in female rats at intravenous doses up to 300 mg/kg/day (0.2 times the recommended human dose based on body surface area), or in male rats at intravenous doses up to 1,000 mg/kg/day. Mating was unaffected in this study.

In a reproduction study of acetylcysteine, male rats were treated orally for 15 weeks prior to mating and during the mating period. A slight non-dose related reduction in fertility was observed at oral doses of 500 and 1,000 mg/kg/day (0.3 and 0.5 times the recommended human intravenous dose, respectively, based on body surface area). Treatment of male rats with acetylcysteine at an oral dose of 250 mg/kg/day for 15 weeks (0.1 times the recommended human intravenous dose based on body surface comparison) did not affect fertility or general reproductive performance.

14 CLINICAL STUDIES

Loading Dose/Infusion Rate Study

A randomized, open-label, multi-center clinical study was conducted in Australia in patients with acetaminophen poisoning to compare the rates of hypersensitivity reactions between two rates of infusion for the intravenous acetylcysteine loading dose. One hundred nine subjects were randomized to a 15-minute infusion rate and seventy-one subjects were randomized to a 60 minute infusion rate. The loading dose was 150 mg/kg followed by a maintenance dose of 50 mg/kg over 4 hours and then 100 mg/kg over 16 hours. Of the 180 patients, 27% were male and 73% were female. Ages ranged from 15 to 83 years, with the mean age being 30 years (±13.0).

A subgroup of 58 subjects (33 in the 15-minute infusion group; 25 in the 60-minute infusion group) was treated within 8 hours of acetaminophen ingestion. No hepatotoxicity occurred within this subgroup; however, with 95% confidence, the true hepatotoxicity rates could range from 0% to 9% for the 15-minute infusion group and from 0% to 12% for the 60-minute infusion group.

Observational Study

An open-label, observational database contained information on 1749 patients who sought treatment for acetaminophen overdose over a 16-year period. Of the 1749 patients, 65% were female, 34% were male and less than 1% was transgender. Ages ranged from 2 months to 96 years, with 72% of the patients falling in the 16- to 40-year-old age bracket. A total of 399 patients received acetylcysteine treatment. A post-hoc analysis identified 56 patients who (1) were at high or probable risk for hepatotoxicity (APAP greater than 150 mg/L at the four hours line according to the Australian nomogram) and (2) had a liver function test. Of the 53 patients who were treated with intravenous acetylcysteine (300 mg/kg intravenous acetylcysteine administered over 20-21 hours) within 8 hours, two (4%) developed hepatotoxicity (AST or ALT greater than 1000 U/L). Twenty-one of 48 (44%) patients treated with acetylcysteine after 15 hours developed hepatotoxicity. The actual number of hepatotoxicity outcomes may be higher than what is reported here. For patients with multiple admissions for acetaminophen overdose, only the first overdose treated with intravenous acetylcysteine was examined. Hepatotoxicity may have occurred in subsequent admissions.

Evaluable data were available from a total of 148 pediatric patients (less than 16 years of age) who were admitted for poisoning following ingestion of acetaminophen, of whom 23 were treated with intravenous acetylcysteine. There were no deaths of pediatric patients. None of the pediatric patients receiving intravenous acetylcysteine developed hepatotoxicity while two patients not receiving intravenous acetylcysteine developed hepatotoxicity. The number of pediatric patients is too small to provide a statistically significant finding of efficacy; however the results appear to be consistent to those observed for adults.

Three-Bag vs. Two-Bag Regimen Observational Study

A multi-center, observational, retrospective cohort study investigated rates of hypersensitivity reactions in 493 patients treated with a two-bag intravenous acetylcysteine regimen compared to 274 patients treated with a three-bag regimen in Denmark between January 2012 and December 2014. The two-bag regimen consisted of a 4 hour loading dose at 200 mg/kg followed by a 16 hour infusion at 100 mg/kg. The three-bag regimen used a 150 mg/kg loading dose administered over 15 minutes, followed by a second dose of 50 mg/kg over 4 hours and a final dose of 100 mg/kg for 16 hours. Patients in this study were treated with acetylcysteine regardless of plasma acetaminophen concentration. The median (range) serum acetaminophen concentration at presentation was <1 mcg/mL (0-353 mcg/mL) in the total study population, and only 12/767 patients (1.6%) had a serum acetaminophen level that would have warranted acetylcysteine treatment based on the revised Rumack-Mathew nomogram.

Hepatotoxicity was defined as peak ALT >1,000 U/L at any point during hospitalization. In this population that was low-risk for hepatotoxicity based on median acetaminophen level at presentation, no differences were observed in unadjusted hepatotoxicity rates between patients who received the two-bag regimen (4%, 20/493) compared to patients who received the three-bag regimen (4%, 11/274). However, this study has significant limitations and was not designed to establish non-inferiority.

16 HOW SUPPLIED/STORAGE AND HANDLING

ACETADOTE (acetylcysteine) injection is available as a 20% solution (200 mg/mL) in 30 mL single-dose glass vials. Each single dose vial contains 6 g/30 mL (200 mg/mL) of ACETADOTE injection. ACETADOTE is sterile and can be used for intravenous administration. It is available as follows:

- 30 mL vials, carton of 4 (NDC 66220-207-30)

Do not use previously opened vials for intravenous administration.

Note: The color of ACETADOTE may turn from essentially colorless to a slight pink or purple once the stopper is punctured. The color change does not affect the quality of the product.

The stopper in the ACETADOTE vial is formulated with a synthetic base-polymer and does not contain natural rubber latex, dry natural rubber, or blends of natural rubber.

Store unopened vials at controlled room temperature, 20° to 25°C (68° to 77°F) [See USP Controlled Room Temperature]

17 PATIENT COUNSELING INFORMATION

Hypersensitivity Reactions

Advise patients and caregivers that hypersensitivity reactions related to administration and infusion may occur during and after ACETADOTE treatment, including hypotension, wheezing, shortness of breath and bronchospasm [see Warnings and Precautions (5.1)].

For specific treatment information regarding the clinical management of acetaminophen overdose, please contact your regional poison center at 1-800-222-1222, or alternatively, a special health professional assistance line for acetaminophen overdose at 1-800-525-6115.

Manufactured for:
Cumberland Pharmaceuticals Inc.
Nashville, TN 37203

U.S. Patent Nos. 8,148,356, 8,399,445, 8,653,061 8,722,738 and 9,327,028

PRINCIPAL DISPLAY PANEL – Vial Label

30 mL NDC 66220-207-30
Sterile

Acetadote®
(acetylcysteine) Injection

6 g/30 mL
(200 mg/mL)

MUST BE FURTHER DILUTED
PRIOR TO INTRAVENOUS USE

CUMBERLAND®

PHARMACEUTICALS

PRINCIPAL DISPLAY PANEL – Carton Label

4 × 30mL Sterile Vials NDC 66220-207-30

Acetadote®
(acetylcysteine) Injection

6 g/30 mL
(200 mg/mL)

MUST BE FURTHER DILUTED
PRIOR TO INTRAVENOUS USE

CUMBERLAND®
PHARMACEUTICALS

Manufactured for:
Cumberland Pharmaceuticals Inc.
Nashville, TN, USA, 37203

Made in USA